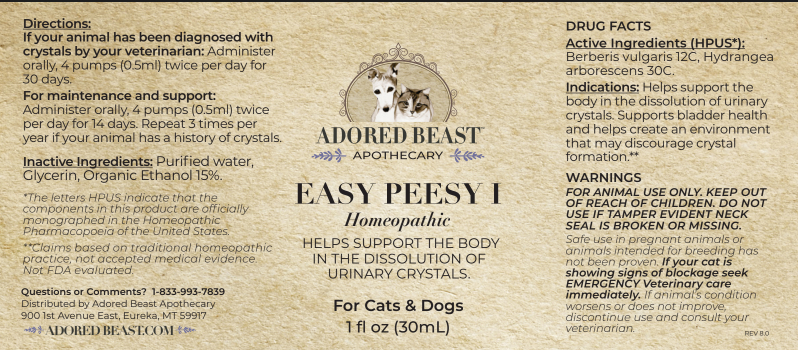 DRUG LABEL: EASY PEESY I
NDC: 86083-0014 | Form: LIQUID
Manufacturer: The Adored Beast Apothecary, Ltd
Category: homeopathic | Type: OTC ANIMAL DRUG LABEL
Date: 20251027

ACTIVE INGREDIENTS: BERBERIS VULGARIS ROOT BARK 12 [hp_C]/30 mL; HYDRANGEA ARBORESCENS ROOT 30 [hp_C]/30 mL
INACTIVE INGREDIENTS: water; GLYCERIN; ALCOHOL

EASY PEESY I

DRUG FACTS
Active Ingredients: Berberis vulgaris 12C, Hydrangea arborescens 30C.

The letters HPUS indicate that the components in this product are officially monographed in the Homeopathic Pharmacopoeia of the United States.
Claims based on traditional homeopathic practice, not accepted medical evidence. Not FDA evaluated.

INDICATIONS AND USAGE

Indications: Helps support the body in the dissolution of urinary crystals. Supports bladder health and helps create an environment that may discourage crystal formation.

WARNINGS
FOR ANIMAL USE ONLY. KEEP OUT OF REACH OF CHILDREN. DO NOT USE IF
TAMPER EVIDENT NECK SEAL IS BROKEN OR MISSING.

KEEP OUT OF REACH OF CHILDREN

DOSAGE AND ADMINISTRATION

If your animal has been diagnosed with crystals by your veterinarian: Administer orally, 4 pumps (0.5ml) twice per day for 30 days.

For maintenance and support: Administer orally, 4 pumps (0.5ml) twice per day for 14 days. Repeat 3 times per year if your animal has a history of crystals.

Inactive Ingredients: Puriﬁed water, Glycerin, Organic Ethanol 15%.

Questions or Comments? 1-833-933-7839

Distributed by Adored Beast Apothecary

900 1st Avenue East, Eureka, MT 59917

OTHER SAFETY INFORMATION

Safe use in pregnant animals or animals intended for breeding has not been proven.

If animal’s condition worsens or does not improve, discontinue use and consult your veterinarian.

If your cat is showing signs of blockage seek EMERGENCY Veterinary care immediately. If animal's condition worsens or does not improve, discontinue use and consult your veterinarian.

PACKAGE LABEL

NDC#: 86083-0014-1

ADORED BEAST

APOTHECARY

EASY PEESY I

Homeopathic

HELPS SUPPORT THE BODY IN THE DISSOLUTION OF URINARY CRYSTALS.

For Cats & Dogs

1 ﬂ oz (30mL)